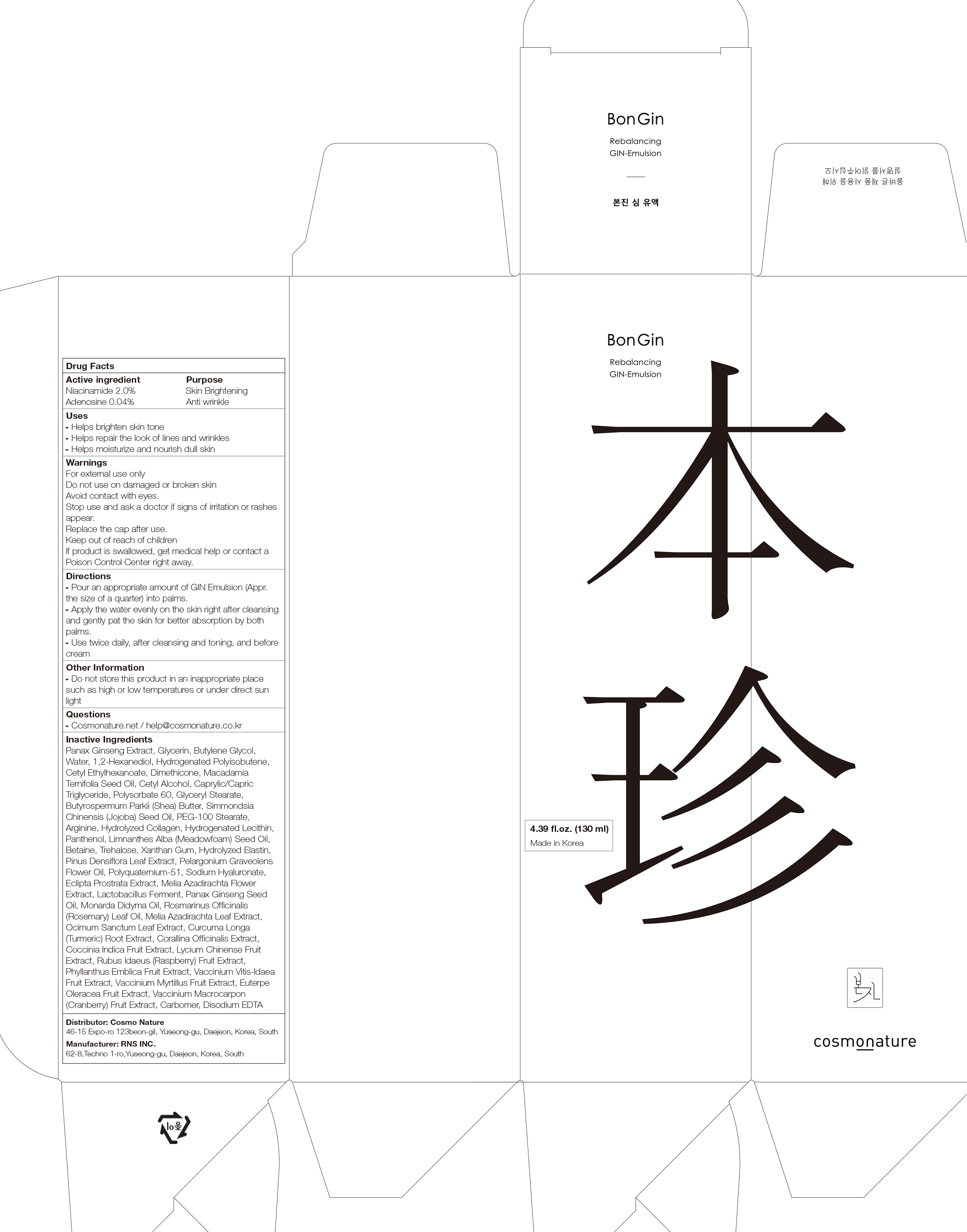 DRUG LABEL: BonGin Rebalancing GIN
NDC: 82492-020 | Form: EMULSION
Manufacturer: Cosmo Nature
Category: otc | Type: HUMAN OTC DRUG LABEL
Date: 20231213

ACTIVE INGREDIENTS: Niacinamide 2.0 g/100 mL; Adenosine 0.04 g/100 mL
INACTIVE INGREDIENTS: Glycerin; Butylene Glycol; Water; 1,2-Hexanediol

ACTIVE INGREDIENTS

Niacinamide 2.0%
Adenosine 0.04%

INACTIVE INGREDIENTS

Panax Ginseng Extract, Glycerin, Butylene Glycol, Water, 1,2-Hexanediol, Hydrogenated Polyisobutene, Cetyl Ethylhexanoate, Dimethicone, Macadamia Ternifolia Seed Oil, Cetyl Alcohol, Caprylic/Capric Triglyceride, Polysorbate 60, Glyceryl Stearate, Butyrospermum Parkii (Shea) Butter, Simmondsia Chinensis (Jojoba) Seed Oil, PEG-100 Stearate, Arginine, Hydrolyzed Collagen, Hydrogenated Lecithin, Panthenol, Limnanthes Alba (Meadowfoam) Seed Oil, Betaine, Trehalose, Xanthan Gum, Hydrolyzed Elastin, Pinus Densiflora Leaf Extract, Pelargonium Graveolens Flower Oil, Polyquaternium-51, Sodium Hyaluronate, Eclipta Prostrata Extract, Melia Azadirachta Flower Extract, Lactobacillus Ferment, Panax Ginseng Seed Oil, Monarda Didyma Oil, Rosmarinus Officinalis (Rosemary) Leaf Oil, Melia Azadirachta Leaf Extract, Ocimum Sanctum Leaf Extract, Curcuma Longa (Turmeric) Root Extract, Corallina Officinalis Extract, Coccinia Indica Fruit Extract, Lycium Chinense Fruit Extract, Rubus Idaeus (Raspberry) Fruit Extract, Phyllanthus Emblica Fruit Extract, Vaccinium Vitis-Idaea Fruit Extract, Vaccinium Myrtillus Fruit Extract, Euterpe Oleracea Fruit Extract, Vaccinium Macrocarpon (Cranberry) Fruit Extract, Carbomer, Disodium EDTA

PURPOSE

Skin Brightening
Anti wrinkle

WARNINGS

For external use only
Do not use on damaged or broken skin
Avoid contact with eyes.
Stop use and ask a doctor if signs of irritation or rashes appear.
Replace the cap after use.
Keep out of reach of children
If product is swallowed, get medical help or contact a Poison Control Center right away.

KEEP OUT OF REACH OF CHILDREN

Uses

■ Helps brighten skin tone
■ Helps repair the look of lines and wrinkles
■ Helps moisturize and nourish dull skin

Directions

■ Pour an appropriate amount of GIN Emulsion (Appr. the size of a quarter) into palms.
■ Apply the water evenly on the skin right after cleansing and gently pat the skin for better absorption by both palms.
■ Use twice daily, after cleansing and toning, and before cream

Other Information

■ Do not store this product in an inappropriate place such as high or low temperatures or under direct sun light

Questions

■ Cosmonature.net / help@cosmonature.co.kr